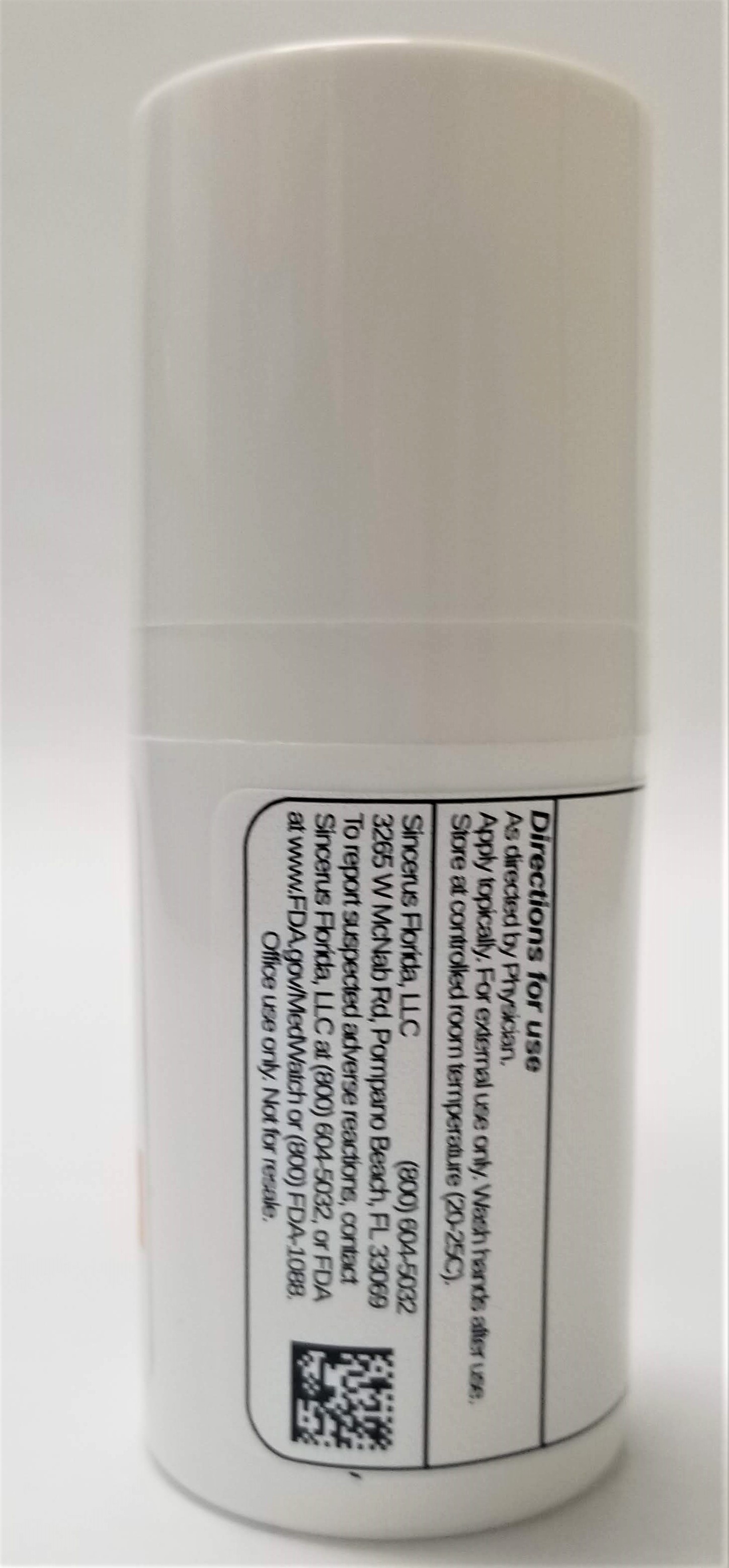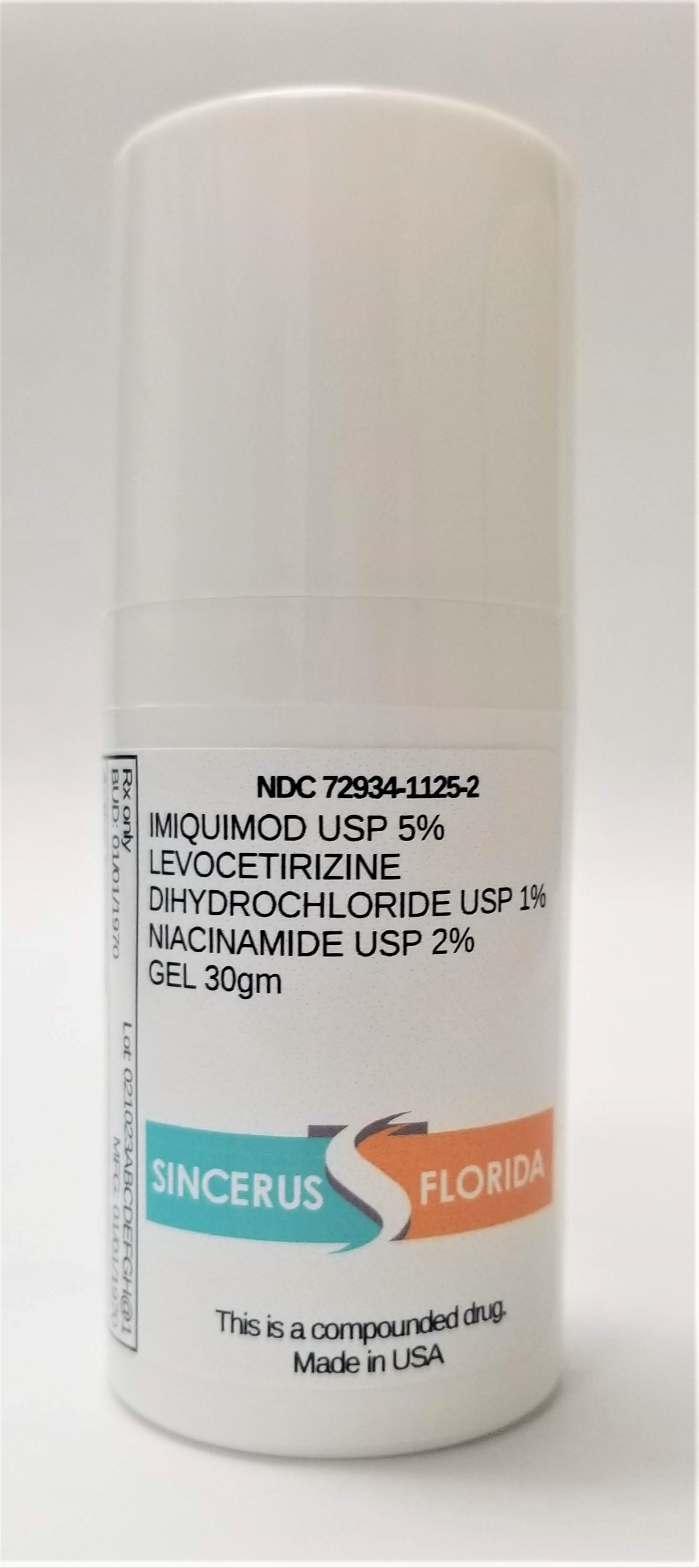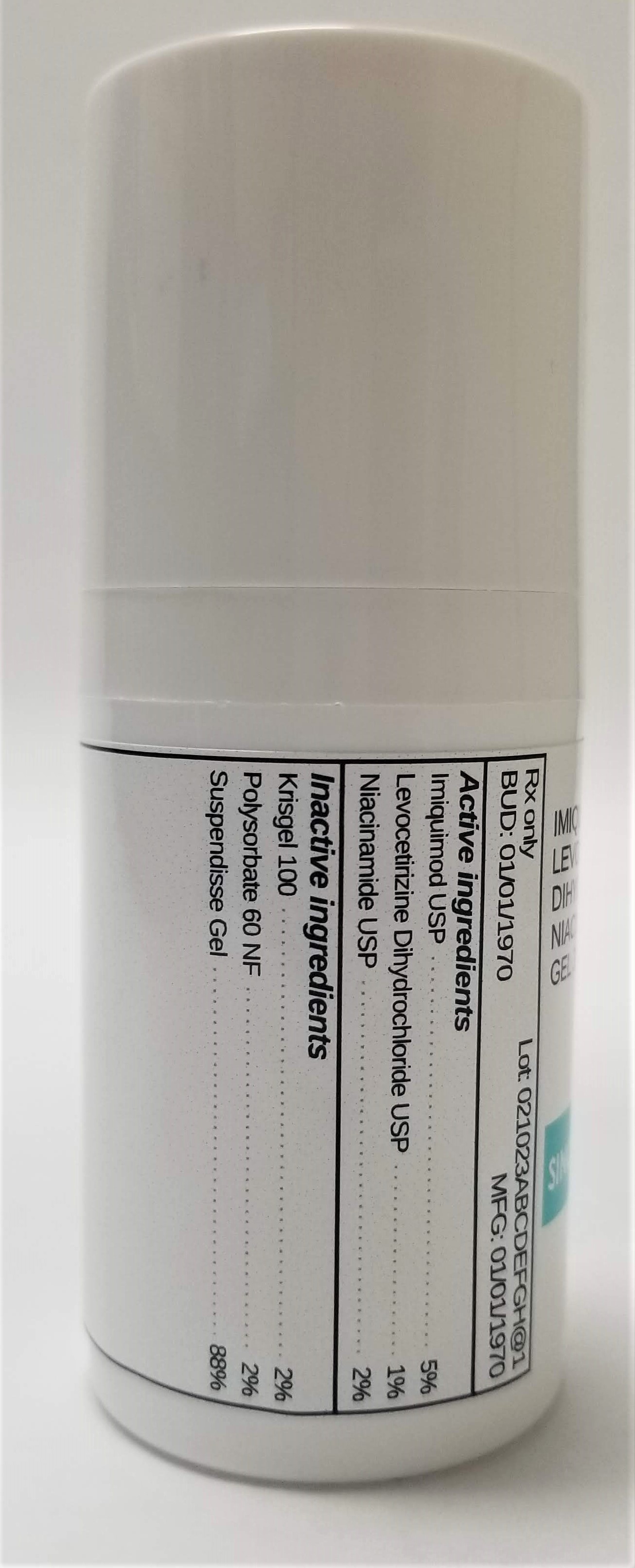 DRUG LABEL: IMIQUIMOD 5% / LEVOCETIRIZINE DIHYDROCHLORIDE 1% / NIACINAMIDE 2%
NDC: 72934-1125 | Form: GEL
Manufacturer: Sincerus Florida, LLC
Category: prescription | Type: HUMAN PRESCRIPTION DRUG LABEL
Date: 20190423

ACTIVE INGREDIENTS: IMIQUIMOD 5 g/100 g; LEVOCETIRIZINE DIHYDROCHLORIDE 1 g/100 g; NIACINAMIDE 2 g/100 g

IMIQUIMOD 5% / LEVOCETIRIZINE DIHYDROCHLORIDE 1% / NIACINAMIDE 2%